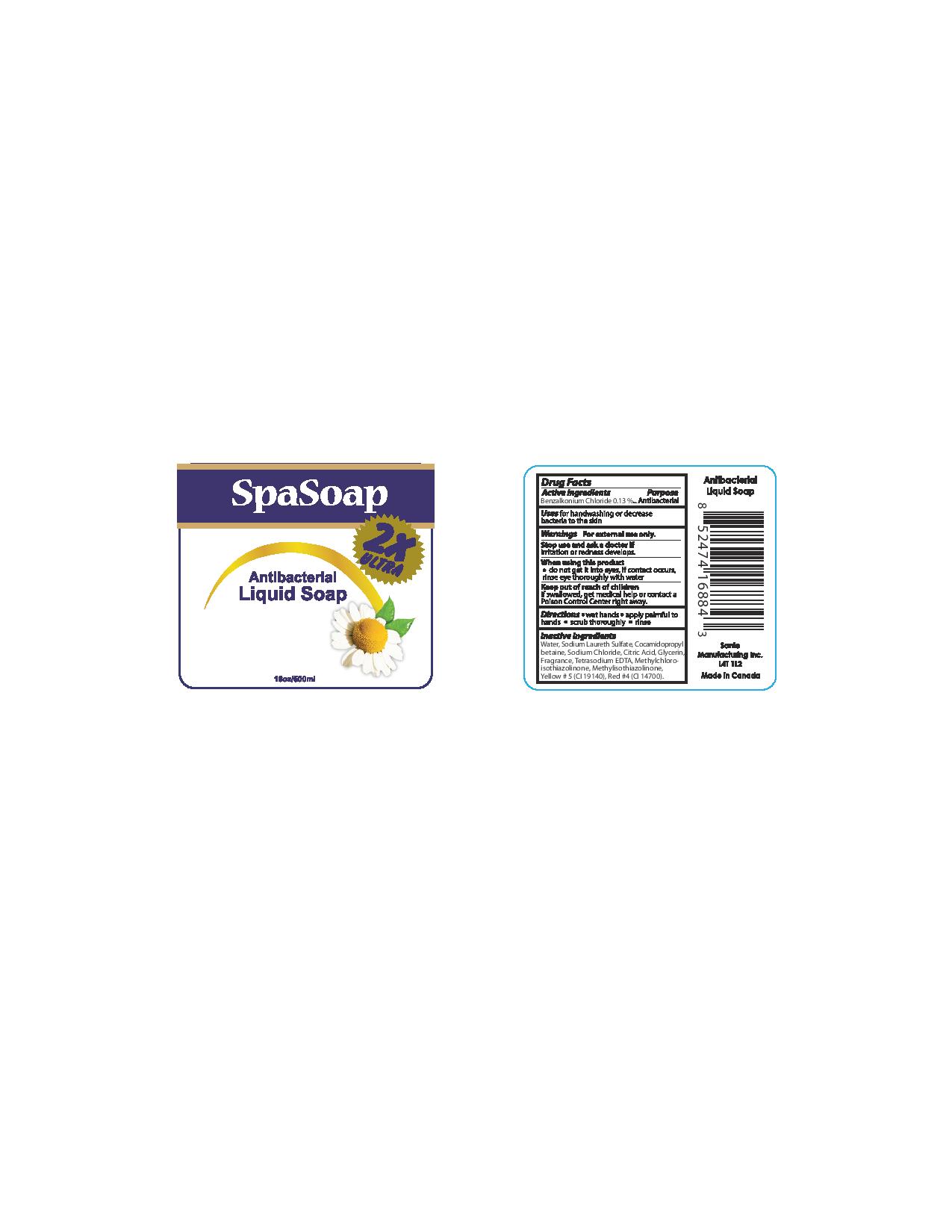 DRUG LABEL: Antibacterial
NDC: 71020-002 | Form: LIQUID
Manufacturer: Sante Manufacturing Inc
Category: otc | Type: HUMAN OTC DRUG LABEL
Date: 20161008

ACTIVE INGREDIENTS: BENZALKONIUM CHLORIDE 1.3 mg/1 mL
INACTIVE INGREDIENTS: DITETRACYCLINE TETRASODIUM EDETATE; FD&C RED NO. 4; WATER; SODIUM CHLORIDE; ANHYDROUS CITRIC ACID; GLYCERIN; METHYLCHLOROISOTHIAZOLINONE; FD&C YELLOW NO. 5; COCAMIDOPROPYL BETAINE; METHYLISOTHIAZOLINONE; SODIUM LAURETH SULFATE

ACTIVE INGREDIENT

Benzalkonium Chloride - 0.13%

Purpose - Antibacterial

INDICATIONS AND USAGE

Uses for handwashing or decrease bacteria to the skin

Stop use and ask a doctor If irritation or redness develops

WARNINGS

Warning for external use only

When using this product

- do not get into eyes. If contact occurs, rinse eyes thoroughly with water

Keep out of reach of children

If swallowed get medical help or contact a Poison Control Center right away

DOSAGE AND ADMINISTRATION

Direction

- Wet hands
- apply palmful to hands
- scrub thoroughly
- rinse

INACTIVE INGREDIENT

Water, Sodium Laureth Sulfate, Cocamidopropyl Betaine, Sodium Chloride, Citric Acid, Glycerin, Tetrasodium EDTA, Methylcholoroisothiazolinone, Methylisothiazolinone, Yellow #5 (Cl 19140), Red #4 (Cl 14700)